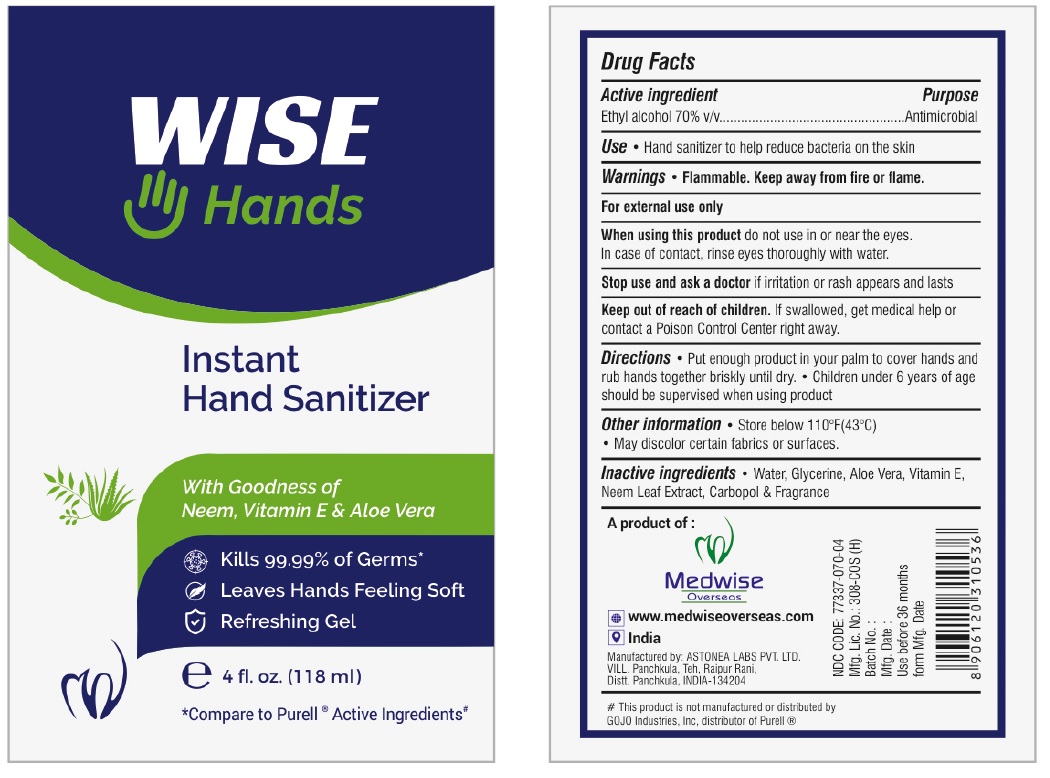 DRUG LABEL: WISE HANDS Instant Hand Sanitizer
NDC: 77337-070 | Form: GEL
Manufacturer: Medwise Overseas Private Limited
Category: otc | Type: HUMAN OTC DRUG LABEL
Date: 20200610

ACTIVE INGREDIENTS: ALCOHOL 70 mL/100 mL
INACTIVE INGREDIENTS: WATER; GLYCERIN; ALOE VERA LEAF; .ALPHA.-TOCOPHEROL; AZADIRACHTA INDICA LEAF; CARBOMER HOMOPOLYMER, UNSPECIFIED TYPE

WISE HANDS Instant Hand Sanitizer

Active ingredient

Ethyl alcohol 70% V/V

Purpose

Antimicrobial

INDICATIONS AND USAGE

Use • Hand sanitizer to help reduce bacteria on the skin

Warnings • Flammable. Keep away from fire or flame.

For external use only

When using this product do not use in or near the eyes. In case of contact, rinse eyes thoroughly with water.

Stop use and ask a doctor if irritation or rash appears and lasts

Keep out of reach of children. If swallowed, get medical help or contact a Poison Control Center right away.

DOSAGE AND ADMINISTRATION

Directions • Put enough product in your palm to cover hands and rub hands together briskly until dry. • Children under 6 years of age should be supervised when using product.

Other information • Store below 110°F(43°C)

• May discolor certain fabrics or surfaces.

INACTIVE INGREDIENT

Inactive ingredients • Water, Glycerine, Aloe Vera, Vitamin E, Neem Leaf Extract, Carbopol & Fragrance

With Goodness of Neem, Vitamin E & Aloe Vera

Kills 99.99% Germs*

Leaves Hands Feeling Soft

Refreshing Gel

*Compare to Purell® Active Ingredients#

www.medwiseoverseas.com

India

Manufactured by: ASTONEA LABS PVT LTD.
VILL. Panchkula, Teh, Rajpur Rani,
Distt. Panchkula, INDIA-134204

#This product is not manufactured or distributed by GOJO Industries, Inc, distributor of Purell®